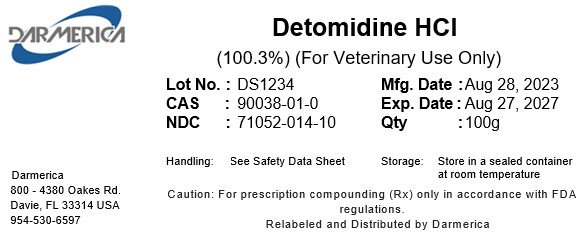 DRUG LABEL: Detomidine HCl
NDC: 71052-014 | Form: POWDER
Manufacturer: DARMERICA, LLC
Category: other | Type: BULK INGREDIENT - ANIMAL DRUG
Date: 20260107

ACTIVE INGREDIENTS: DETOMIDINE HYDROCHLORIDE 1 kg/1 kg

Detomidine HCl